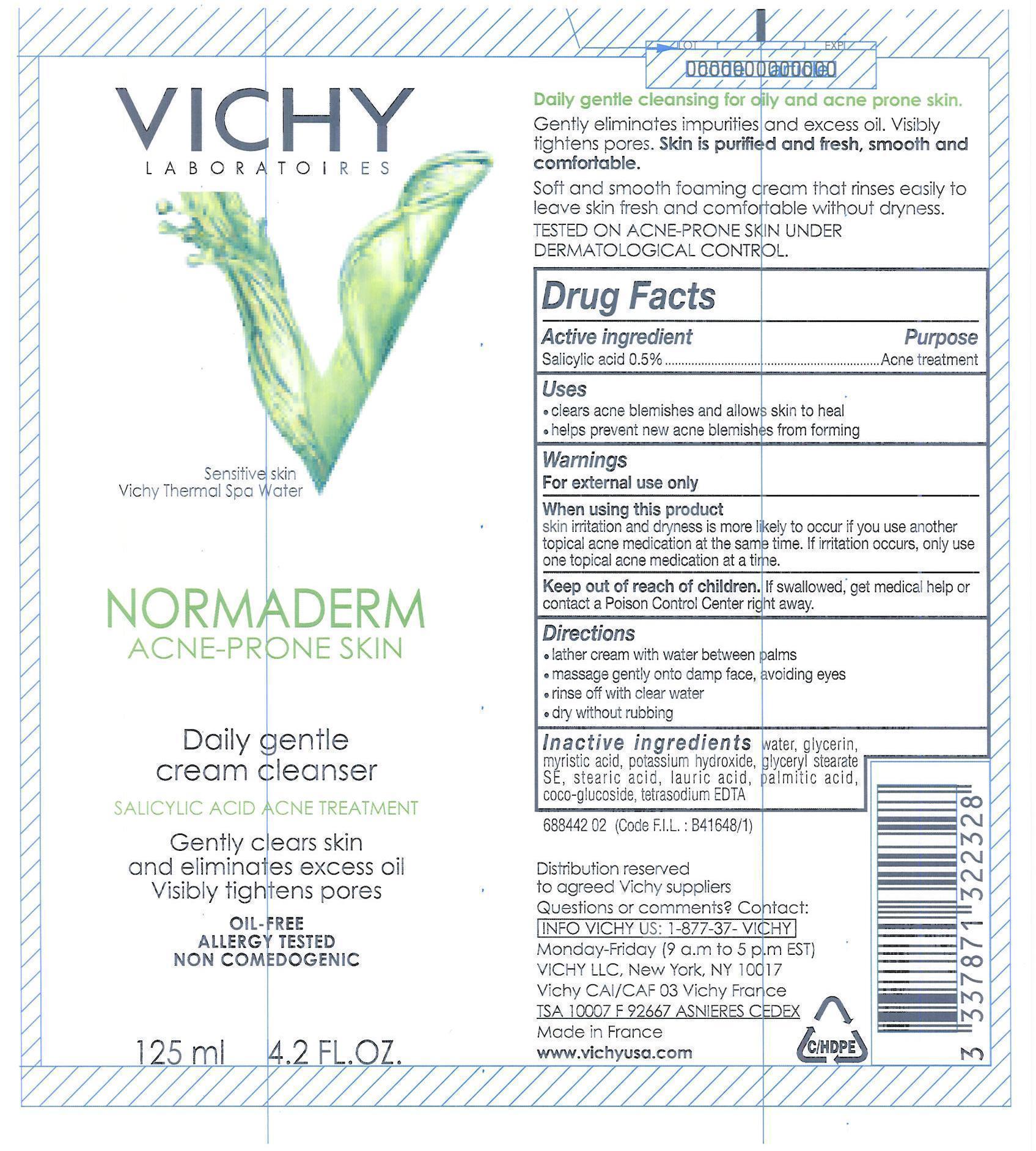 DRUG LABEL: Vichy Laboratoires Normaderm Daily Gentle Cleanser
NDC: 49967-232 | Form: CREAM
Manufacturer: L'Oreal USA Products Inc
Category: otc | Type: HUMAN OTC DRUG LABEL
Date: 20240101

ACTIVE INGREDIENTS: Salicylic Acid 5 mg/1 mL
INACTIVE INGREDIENTS: WATER; GLYCERIN; MYRISTIC ACID; POTASSIUM HYDROXIDE; GLYCERYL STEARATE SE; STEARIC ACID; LAURIC ACID; PALMITIC ACID; COCO GLUCOSIDE; EDETATE SODIUM

Drug Facts

Active ingredient

Salicylic acid...0.5%

Purpose

Acne treatment

Uses

- clears acne blemishes and allows skin to heal
- helps prevent new acne blemishes from forming

Warnings

For external use only

When using this product skin irritation and dryness is more likely to occur if you use another topical acne medication at the same time. if irritation occurs, only use one topical acne medication at a time.

Keep out of reach of children. If swallowed, get medical help or contact a Poison Control Center right away.

Directions

- lather cream with water between palms
- massage gently onto damp face, avoiding eyes
- rinse off with clear water
- dry without rubbing

Inactive ingredients

water, glycerin, myristic acid, potassium hydroxide, glyceryl stearate SE, stearic acid, lauric acid, palmitic acid, coco-glucoside, tetrasodium EDTA

Keep out of reach of children.

If swallowed, get medical help or contact a Poison Control Center right away.